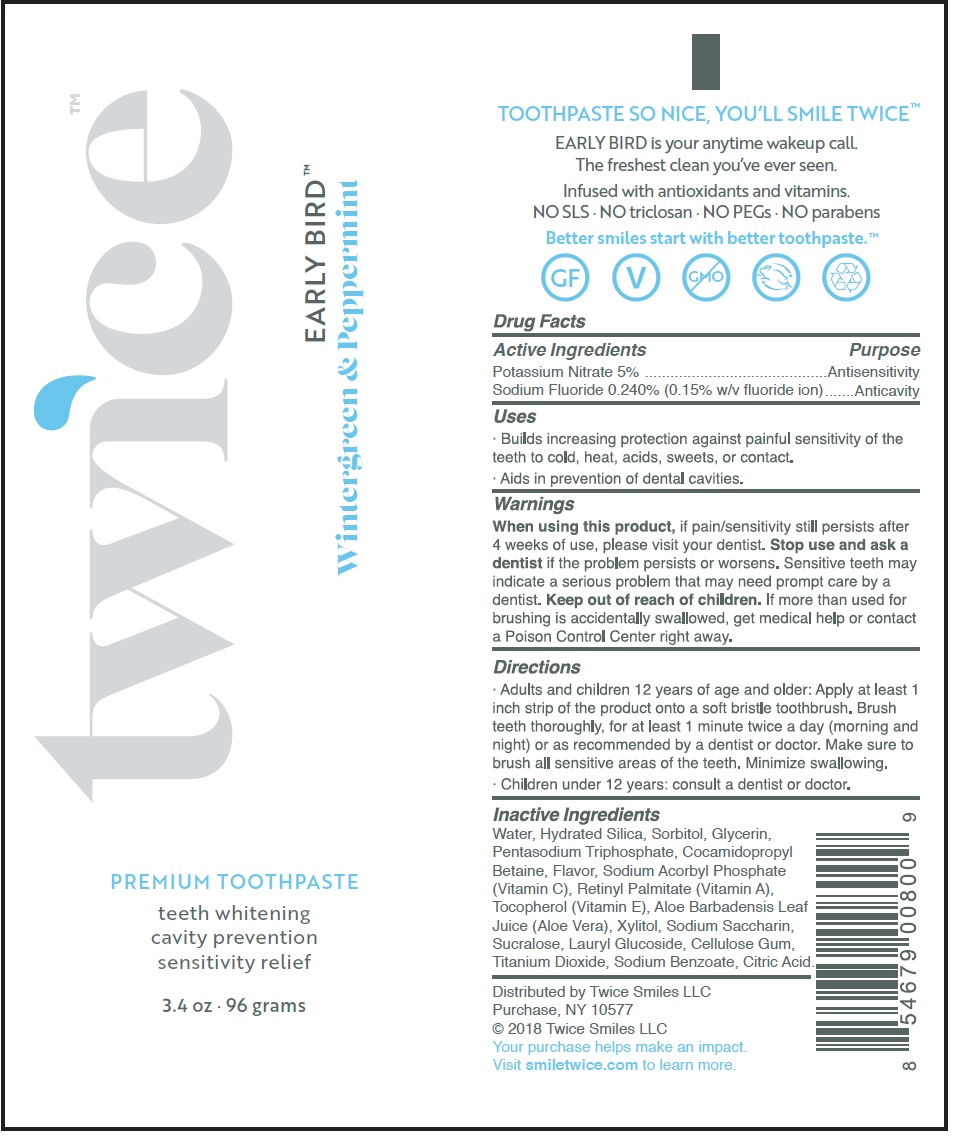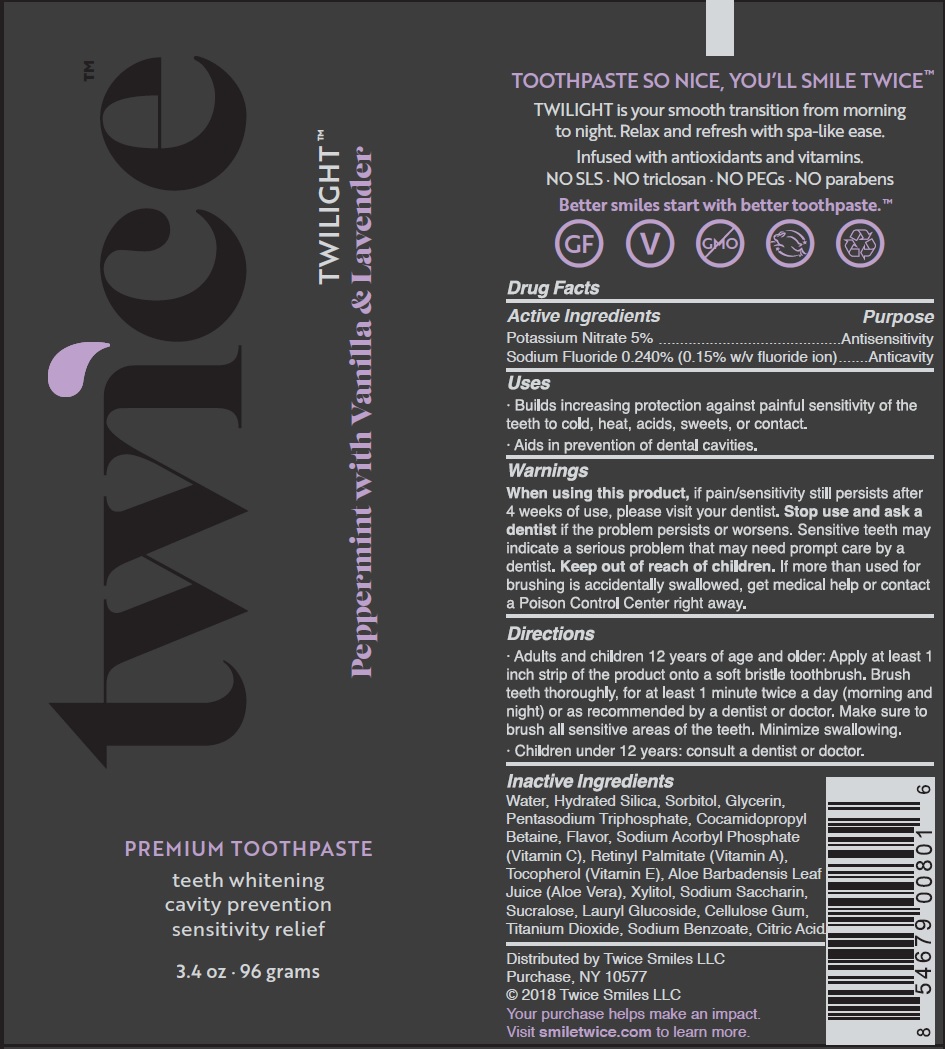 DRUG LABEL: The Duo
NDC: 72164-100 | Form: KIT | Route: DENTAL
Manufacturer: Smiletwice, Inc.
Category: otc | Type: HUMAN OTC DRUG LABEL
Date: 20231221

ACTIVE INGREDIENTS: POTASSIUM NITRATE 50 mg/1 g; SODIUM FLUORIDE 2.4 mg/1 g; POTASSIUM NITRATE 50 mg/1 g; SODIUM FLUORIDE 2.4 mg/1 g
INACTIVE INGREDIENTS: VITAMIN A PALMITATE; TOCOPHEROL; ALOE VERA LEAF; XYLITOL; SACCHARIN SODIUM; SUCRALOSE; LAURYL GLUCOSIDE; CARBOXYMETHYLCELLULOSE SODIUM, UNSPECIFIED FORM; TITANIUM DIOXIDE; SODIUM BENZOATE; CITRIC ACID MONOHYDRATE; GLYCERIN; WATER; HYDRATED SILICA; SORBITOL; SODIUM TRIPOLYPHOSPHATE ANHYDROUS; COCAMIDOPROPYL BETAINE; METHYL SALICYLATE; SODIUM ASCORBYL PHOSPHATE; WATER; HYDRATED SILICA; SORBITOL; GLYCERIN; SODIUM TRIPOLYPHOSPHATE ANHYDROUS; COCAMIDOPROPYL BETAINE; METHYL SALICYLATE; SODIUM ASCORBYL PHOSPHATE; VITAMIN A PALMITATE; TOCOPHEROL; ALOE VERA LEAF; XYLITOL; SACCHARIN SODIUM; SUCRALOSE; LAURYL GLUCOSIDE; CARBOXYMETHYLCELLULOSE SODIUM, UNSPECIFIED FORM; TITANIUM DIOXIDE; SODIUM BENZOATE; CITRIC ACID MONOHYDRATE

The Duo

Active ingredients

Potassium Nitrate 5% Sodium Fluoride 0.240% (0.15% w/v Fluoride ion)

Purpose

Antihypersensitivity

Anticavity

Uses

Builds increasing protection against painful sensitivity of the teeth to cold, heat, acids, sweets, or contact. Aids in prevention of dental cavities.

Warnings

When using this product,

if pain/sensitivity still persists after 4 weeks of use, please visit your dentist.

Stop use and ask a dentist

if the problem persists or worsens. Sensitive teeth may indicate a serious problem that may need prompt care by a dentist.

Keep out of reach of children.

If more than used for brushing is accidentally swallowed, get medical help or contact a Poison Control Center right away.

Directions

Adults and children 12 years of age and older: Apply at least 1 inch strip of the product onto a soft bristle toothbrush. Brush teeth thoroughly, for at least 1 minute twice a day (morning and night) or as recommended by a dentist or doctor. Make sure to brush all sensitive areas of the teeth. Minimize swallowing. · Children under 12 years: consult a dentist or doctor.

Inactive Ingredients

Water, Hydrated Silica, Sorbitol, Glycerin, Pentasodium Triphosphate, Cocamidopropyl Betaine, Flavor, Sodium Ascorbyl Phosphate (Vitamin C), Retinyl Palmitate (Vitamin A),Tocopherol (Vitamin E), Aloe Barbadensis Leaf Juice (Aloe Vera), Xylitol, Sodium Saccharin, Sucralose, Lauryl Glucoside, Cellulose Gum, Titanium Dioxide, Sodium Benzoate, Citric Acid.

Active ingredients

Potassium Nitrate 5% Sodium Fluoride 0.240% (0.15% w/v Fluoride ion)

Purpose

Antihypersensitivity

Anticavity

Uses

Builds increasing protection against painful sensitivity of the teeth to cold, heat, acids, sweets, or contact. Aids in prevention of dental cavities.

Warnings

When using this product

if pain/sensitivity still persists after 4 weeks of use, please visit your dentist.

Stop use and ask a dentist

if the problem persists or worsens. Sensitive teeth may indicate a serious problem that may need prompt care by a dentist.

Keep out of reach of children.

If more than used for brushing is accidentally swallowed, get medical help or contact a Poison Control Center right away.

Directions

Adults and children 12 years of age and older: Apply at least 1 inch strip of the product onto a soft bristle toothbrush. Brush teeth thoroughly, for at least 1 minute twice a day (morning and night) or as recommended by a dentist or doctor. Make sure to brush all sensitive areas of the teeth. Minimize swallowing. · Children under 12 years: consult a dentist or doctor.

Inactive Ingredients

Water, Hydrated Silica, Sorbitol, Glycerin, Pentasodium Triphosphate, Cocamidopropyl Betaine, Flavor, Sodium Acorbyl Phosphate (Vitamin C), Retinyl Palmitate (Vitamin A), Tocopherol (Vitamin E), Aloe Barbadensis Leaf Juice (Aloe Vera), Xylitol, Sodium Saccharin, Sucralose, Lauryl Glucoside, Cellulose Gum, Titanium Dioxide, Sodium Benzoate, Citric Acid.